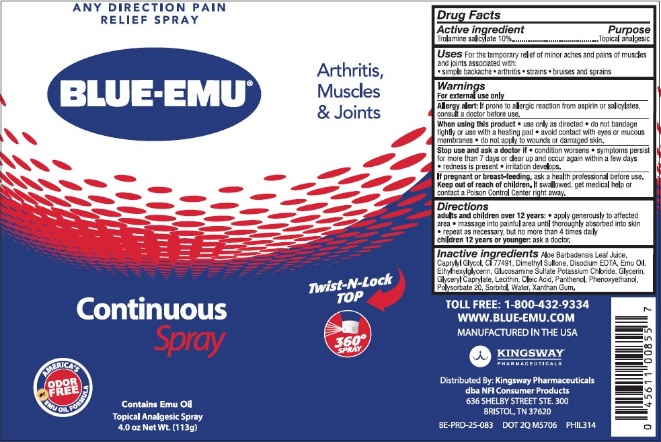 DRUG LABEL: Maximum Strength Blue Emu Pain Relief
NDC: 69993-100 | Form: SPRAY
Manufacturer: Kingsway Pharmaceuticals dba NFI, LLC
Category: otc | Type: HUMAN OTC DRUG LABEL
Date: 20250131

ACTIVE INGREDIENTS: Trolamine Salicylate 10 g/100 mL
INACTIVE INGREDIENTS: ALOE VERA LEAF; CAPRYLYL GLYCOL; FERRIC OXIDE RED; DIMETHYL SULFONE; EDETATE DISODIUM; EMU OIL; ETHYLHEXYLGLYCERIN; GLUCOSAMINE SULFATE POTASSIUM CHLORIDE; GLYCERIN; GLYCERYL MONOCAPRYLATE; SOYBEAN LECITHIN; OLEIC ACID; Panthenol; Phenoxyethanol; Polysorbate 20; SORBITOL; Water; Xanthan Gum

Maximum Strength Blue Emu® Pain Relief Spray

Active ingredient

Trolamine salicylate 10%

Purpose

Topical analgesic

Uses

For the temporary relief of minor aches and pains of muscles and joints associated with:

- simple backache
- arthritis
- strains
- bruises and sprains

Warnings

For external use only

Allergy alert:

If prone to allergic reaction from aspirin or salicylates, consult a doctor before use.

When using this product

- use only as directed
- do not bandage tightly or use with a heating pad
- avoid contact with eyes or mucous membranes
- do not apply to wounds or damaged skin.

Stop use and ask a doctor if

- condition worsens
- symptoms persist for more than 7 days or clear up and occur again within a few days
- redness is present
- irritation develops.

PREGNANCY OR BREAST FEEDING

If pregnant or breast-feeding, ask a health professional before use.

Keep out of reach of children. If swallowed, get medical help or contact a Poison Control Center right away.

Directions

adults and children over 12 years:

- apply generously to affected area
- massage into painful area until thoroughly absorbed into skin
- repeat as necessary, but no more than 4 times daily

children 12 years or younger: ask a doctor.

Inactive ingredients

Aloe Barbadensis Leaf Juice, Caprylyl Glycol, CI 77491, Dimethyl Sulfone, Disodium EDTA, Emu Oil, Ethylhexylglycerin, Glucosamine Sulfate Potassium Chloride, Glycerin, Glyceryl Caprylate, Lecithin, Oleic Acid, Panthenol, Phenoxyethanol, Polysorbate 20, Sorbitol, Water, Xanthan Gum.

TOLL FREE: 1-800-432-9334
WWW.BLUE-EMU.COM
MANUFACTURED IN THE USA
KINGSWAY™
PHARMACEUTICALS
Distributed By: Kingsway Pharmaceuticals
dba NFI Consumer Products
636 SHELBY STREET STE. 300
BRISTOL, TN 37620

PRINCIPAL DISPLAY PANEL - Can Label

ANY DIRECTION PAIN
RELIEF SPRAY
Arthritis,
Muscles
& Joints
BLUE-EMU®
Continuous
Spray
Twist-N-Lock
TOP
360º Spray
AMERICA'S
#1
EMU OIL FORMULA
ODOR
FREE
Contains Emu Oil
Topical Analgesic Spray
4.0 oz Net Wt. (113g)